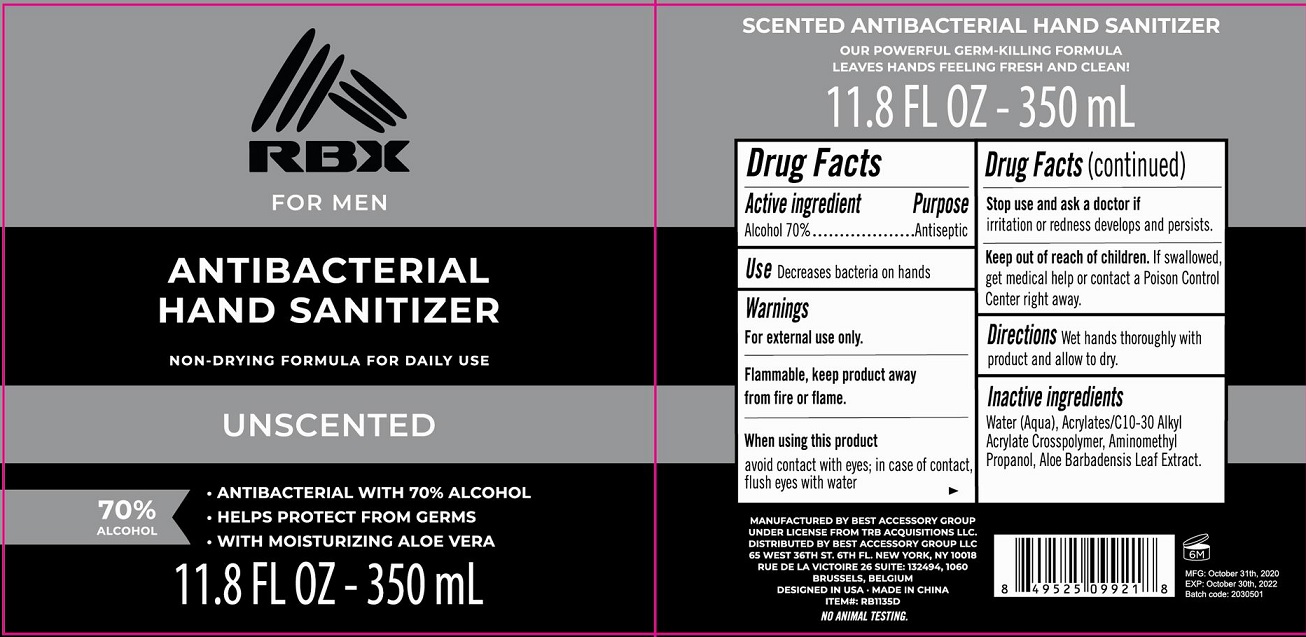 DRUG LABEL: RBX For Men Antibacterial Hand Sanitizer Unscented
NDC: 56136-506 | Form: LIQUID
Manufacturer: Ganzhou Olivee Cosmetic Co., Ltd.
Category: otc | Type: HUMAN OTC DRUG LABEL
Date: 20201116

ACTIVE INGREDIENTS: ALCOHOL 70 mL/100 mL
INACTIVE INGREDIENTS: WATER; CARBOMER COPOLYMER TYPE A; AMINOMETHYLPROPANOL; ALOE VERA LEAF

Active ingredient

Alcohol 70%

Purpose

Antiseptic

Use

Decrease bacteria on hands

Warnings

For external use only.

When using this product

avoid contact with eyes; in case of contact, flush eyes with water.

Stop use and ask a doctor if

- irritation and redness develops and persists.

Keep out of reach of children.

If swallowed, get medical help or contact a Poison Control Center right away.

Directions

Apply onto wet hands working into a lather. Rinse thorougly.

Inactive ingredients

Water (Aqua), Acrylates/C10-30 Alkyl Acrylate Crosspolymer, Aminomethyl Propanol, Aloe Barbadensis Leaf Extract.